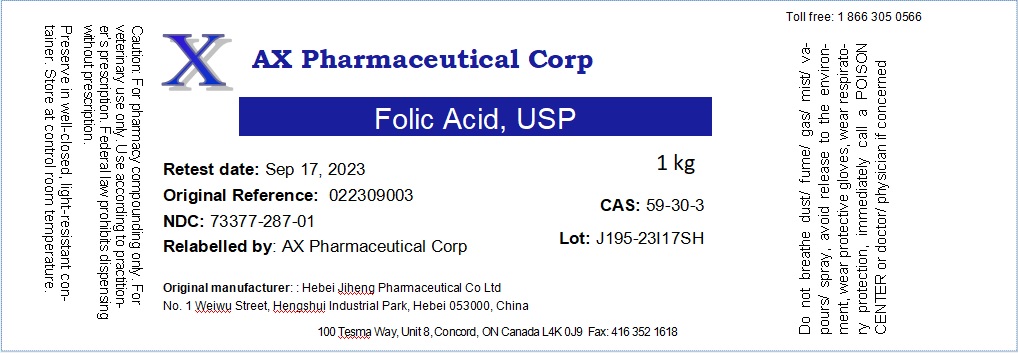 DRUG LABEL: Folic Acid
NDC: 73377-287 | Form: POWDER
Manufacturer: AX Pharmaceutical Corp
Category: other | Type: BULK INGREDIENT - ANIMAL DRUG
Date: 20241230

ACTIVE INGREDIENTS: FOLIC ACID 1 g/1 g

Folic Acid